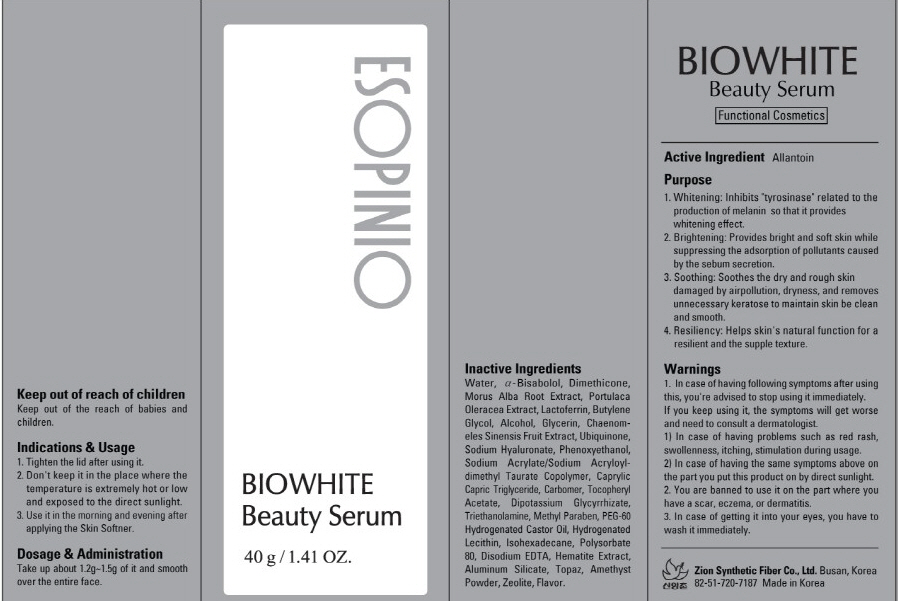 DRUG LABEL: BIOWHITE BEAUTY SERUM
NDC: 44781-130 | Form: CREAM
Manufacturer: ZION SYNTHETIC FIBER CO., LTD.
Category: otc | Type: HUMAN OTC DRUG LABEL
Date: 20110829

ACTIVE INGREDIENTS: ALLANTOIN 0.2 g/40 g
INACTIVE INGREDIENTS: Water; LEVOMENOL; Dimethicone; MORUS ALBA POLLEN; Butylene Glycol; Alcohol; Glycerin; UBIDECARENONE; HYALURONATE SODIUM; Phenoxyethanol; MEDIUM-CHAIN TRIGLYCERIDES; CARBOMER 934; TROLAMINE; METHYLPARABEN; POLYOXYL 60 HYDROGENATED CASTOR OIL; Polysorbate 80; EDETATE DISODIUM; Aluminum Silicate

Drug Facts

Active ingredient: ALLANTOIN

Inactive ingredients:

Water, Alpha Bisabolol, Dimethicone, Morus Alba Root Extract, Portulaca Oleracea Extract, Lactoferrin, Butylene Glycol, Alcohol, Glycerin, Chaenomeles Sinensis Fruit Extract, Ubiquinone, Sodium Hyaluronate, Phenoxyethanol, Sodium Acrylate/Sodium Acryloyldimethyl Taurate Copolymer, Caprylic Capric Triglyceride, Carbomer, Tocopheryl Acetate, Dipotassium Glycyrrhizate, Triethanolamine, Methyl Paraben, PEG-60 Hydrogenated Castor Oil, Hydrogenated Lecithin, Isohexadecane, Polysorbate 80, Disodium EDTA, Hematite Extract, Aluminum Silicate, Topaz, Amethyst Powder, Zeolite, Flavor

Purpose:
It inhibits tyrosinase related to the production of melanin so that it provides whitening effect and provides bright and soft skin while suppressing the adsorption of pollutants caused by the sebum secretion.
It helps skin's natural function for a resilient and the supple texture.

Warnings:
In case of having following symptoms after using this, you're advised to stop using it immediately. If you keep using it, the symptoms will get worse and need to consult a dermatologist.
- In case of having problems such as red rash, swollenness, itching, stimulation during usage.
- In case of having the same symptoms above on the part you put this product on by direct sunlight.
You are banned to use it on the part where you have a scar, eczema, or dermatitis.
In case of getting it into your eyes, you have to wash it immediately.

Keep out of reach of children:
Keep out of the reach of babies and children.

Indications and Usage:
Tighten the lid after using it.
Don't keep it in the place where the temperature is extremely hot or low and exposed to the direct sunlight.
Use it in the morning and evening after applying the Skin Softner.

Dosage and administration:
Take up about 2 - 3 drops of it, and smooth over the entire face, in the morning and evening.